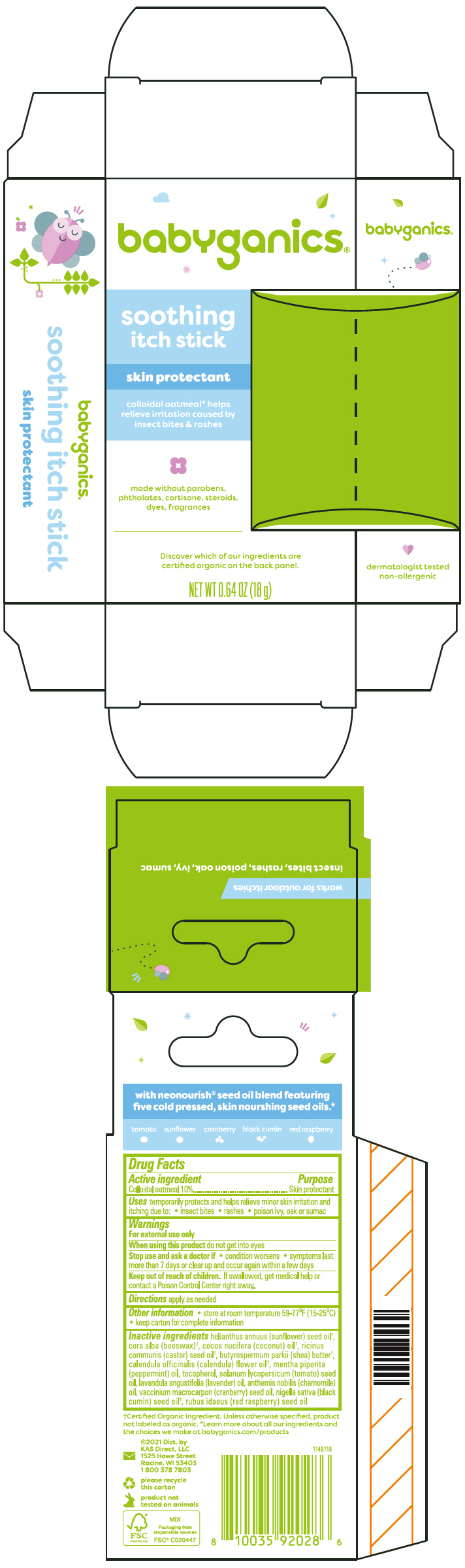 DRUG LABEL: Babyganics Soothing Itch
NDC: 59062-3301 | Form: STICK
Manufacturer: KAS Direct, LLC
Category: otc | Type: HUMAN OTC DRUG LABEL
Date: 20240828

ACTIVE INGREDIENTS: OATMEAL 100 mg/1 g
INACTIVE INGREDIENTS: SUNFLOWER SEED; WHITE WAX; COCONUT OIL; CASTOR OIL; SHEA BUTTER; CALENDULA OFFICINALIS FLOWER; PEPPERMINT OIL; Tocopherol; TOMATO SEED OIL; LAVENDER OIL; CHAMAEMELUM NOBILE FLOWER OIL; CRANBERRY SEED OIL; NIGELLA SATIVA SEED OIL; RASPBERRY SEED OIL

Babyganics® Soothing Itch Stick

Drug Facts

Active ingredient

Colloidal oatmeal 10%

Purpose

Skin protectant

Uses

temporarily protects and helps relieve minor skin irritation and itching due to:

- insect bites
- rashes
- poison ivy, oak or sumac

Warnings

For external use only

When using this product do not get into eyes

Stop use and ask a doctor if

- condition worsens
- symptoms last more than 7 days or clear up and occur again within a few days

Keep out of reach of children. If swallowed, get medical help or contact a Poison Control Center right away.

Directions

apply as needed

Other information

- store at room temperature 59-77°F (15-25°C)
- keep carton for complete information

Inactive ingredients

helianthus annuus (sunflower) seed oil [Certified Organic Ingredient. Unless otherwise specified, product not labeled as organic.] , cera alba (beeswax), cocos nucifera (coconut) oil, ricinus communis (castor) seed oil, butyrospermum parkii (shea) butter, calendula officinalis (calendula) flower oil, mentha piperita (peppermint) oil, tocopherol, solanum lycopersicum (tomato) seed oil, lavandula angustifolia (lavender) oil, anthemis nobilis (chamomile) oil,vaccinium macrocarpon (cranberry) seed oil, nigella sativa (black cumin) seed oil, rubus idaeus (red raspberry) seed oil

Dist. by
KAS Direct, LLC
1525 Howe Street
Racine, WI 53403

PRINCIPAL DISPLAY PANEL - 18 g Stick Carton

babyganics®

soothing
itch stick

skin protectant

colloidal oatmeal* helps
relieve irritation caused by
insect bites & rashes

made without parabens,
phthalates, cortisone, steroids,
dyes, fragrances

Discover which of our ingredients are
certified organic on the back panel.

NET WT 0.64 OZ (18 g)